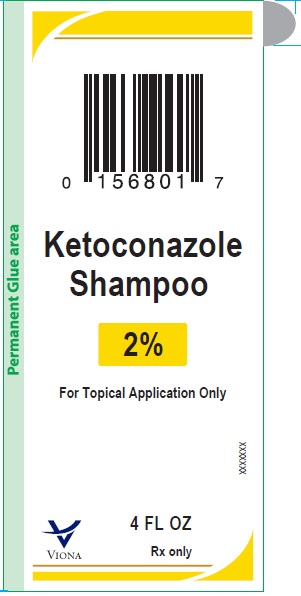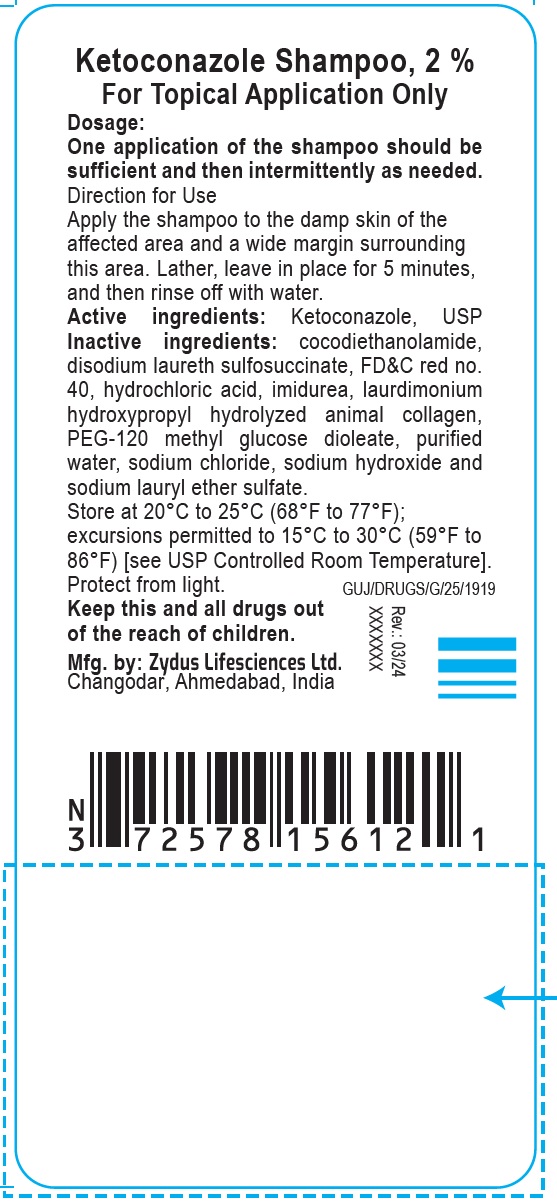 DRUG LABEL: Ketoconazole
NDC: 70771-1874 | Form: SHAMPOO
Manufacturer: Zydus Lifesciences Limited
Category: prescription | Type: HUMAN PRESCRIPTION DRUG LABEL
Date: 20250312

ACTIVE INGREDIENTS: KETOCONAZOLE 20 mg/1 mL
INACTIVE INGREDIENTS: COCO DIETHANOLAMIDE; DISODIUM LAURETH SULFOSUCCINATE; FD&C RED NO. 40; HYDROCHLORIC ACID; IMIDUREA; PEG-120 METHYL GLUCOSE DIOLEATE; SODIUM CHLORIDE; SODIUM LAURETH-3 SULFATE; WATER

Ketoconazole Shampoo, 2%

PACKAGE LABEL.PRINCIPAL DISPLAY PANEL

NDC 70771-1874-7

Ketoconazole Shampoo, 2%

For Topical Application Only

4 FL OZ (120 mL)

Rx Only

Front Image
Back image